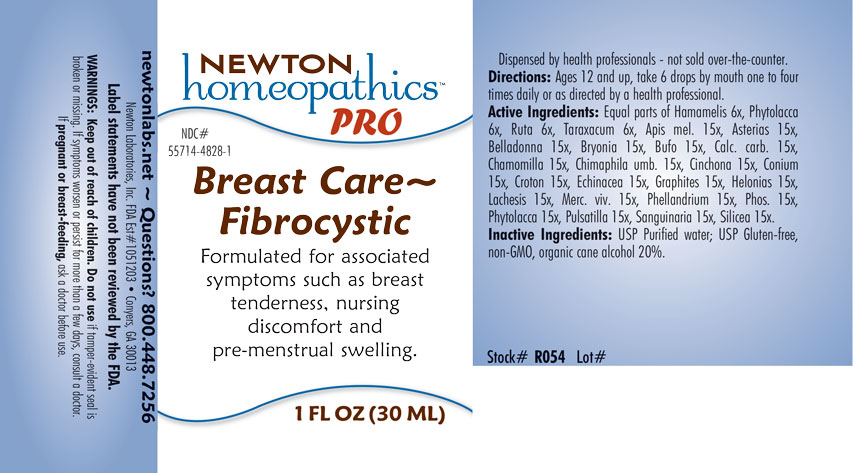 DRUG LABEL: Breast Care - Fibrocystic
NDC: 55714-4828 | Form: LIQUID
Manufacturer: Newton Laboratories, Inc.
Category: homeopathic | Type: HUMAN OTC DRUG LABEL
Date: 20201202

ACTIVE INGREDIENTS: BUFO BUFO CUTANEOUS GLAND 15 [hp_X]/1 mL; APIS MELLIFERA 15 [hp_X]/1 mL; ASTERIAS RUBENS 15 [hp_X]/1 mL; ATROPA BELLADONNA 15 [hp_X]/1 mL; BRYONIA ALBA ROOT 15 [hp_X]/1 mL; OYSTER SHELL CALCIUM CARBONATE, CRUDE 15 [hp_X]/1 mL; MATRICARIA CHAMOMILLA 15 [hp_X]/1 mL; CHIMAPHILA UMBELLATA 15 [hp_X]/1 mL; CINCHONA OFFICINALIS BARK 15 [hp_X]/1 mL; CONIUM MACULATUM FLOWERING TOP 15 [hp_X]/1 mL; CROTON TIGLIUM SEED 15 [hp_X]/1 mL; ECHINACEA, UNSPECIFIED 15 [hp_X]/1 mL; GRAPHITE 15 [hp_X]/1 mL; CHAMAELIRIUM LUTEUM ROOT 15 [hp_X]/1 mL; LACHESIS MUTA VENOM 15 [hp_X]/1 mL; MERCURY 15 [hp_X]/1 mL; OENANTHE AQUATICA FRUIT 15 [hp_X]/1 mL; PHOSPHORUS 15 [hp_X]/1 mL; PHYTOLACCA AMERICANA ROOT 15 [hp_X]/1 mL; ANEMONE PULSATILLA 15 [hp_X]/1 mL; SANGUINARIA CANADENSIS ROOT 15 [hp_X]/1 mL; SILICON DIOXIDE 15 [hp_X]/1 mL; HAMAMELIS VIRGINIANA ROOT BARK/STEM BARK 6 [hp_X]/1 mL; RUTA GRAVEOLENS FLOWERING TOP 6 [hp_X]/1 mL; TARAXACUM OFFICINALE 6 [hp_X]/1 mL
INACTIVE INGREDIENTS: WATER; ALCOHOL

Breast 4828L

INDICATIONS & USAGE SECTION

Formulated for associated symptoms such as breast tenderness, nursing discomfort and pre-menstrual swelling.

DOSAGE & ADMINISTRATION SECTION

Directions: Ages 12 and up take 6 drops by mouth one to four times daily or as directed by a health professional.

OTC - ACTIVE INGREDIENT SECTION

Equal parts of Hamamelis 6x, Phytolacca 6x, Ruta 6x, Taraxacum 6x, Apis mel. 15x, Asterias 15x, Belladonna 15x, Bryonia 15x, Bufo 15x, Calc. carb. 15x, Chamomilla 15x, Chimaphila umb. 15x, Cinchona 15x, Conium 15x, Croton 15x, Echinacea 15x, Graphites 15x, Helonias 15x, Lachesis 15x, Merc. viv. 15x, Phellandrium 15x, Phos. 15x, Phytolacca 15x, Pulsatilla 15x, Sanguinaria 15x, Silicea 15x.

INACTIVE INGREDIENT SECTION

Inactive Ingredients: USP Purified water; USP Gluten-free, non-GMO, organic cane alcohol 20%.

QUESTIONS SECTION

newtonlabs.net - Questions? 800 448-7256

Newton Laboratories, Inc. FDA Est. # 1051203 - Conyers, GA 30013

WARNINGS SECTION

WARNINGS: Keep out of reach of children. Do not use if tamper-evident seal is broken or missing. If symptoms worsen or persist for more than a few days, consult a doctor. If pregnant or breast-feeding, ask a doctor before use.

OTC - PREGNANCY OR BREAST FEEDING SECTION

If pregnant or breast-feeding, ask a doctor before use.

OTC - KEEP OUT OF REACH OF CHILDREN SECTION

Keep out of reach of children.